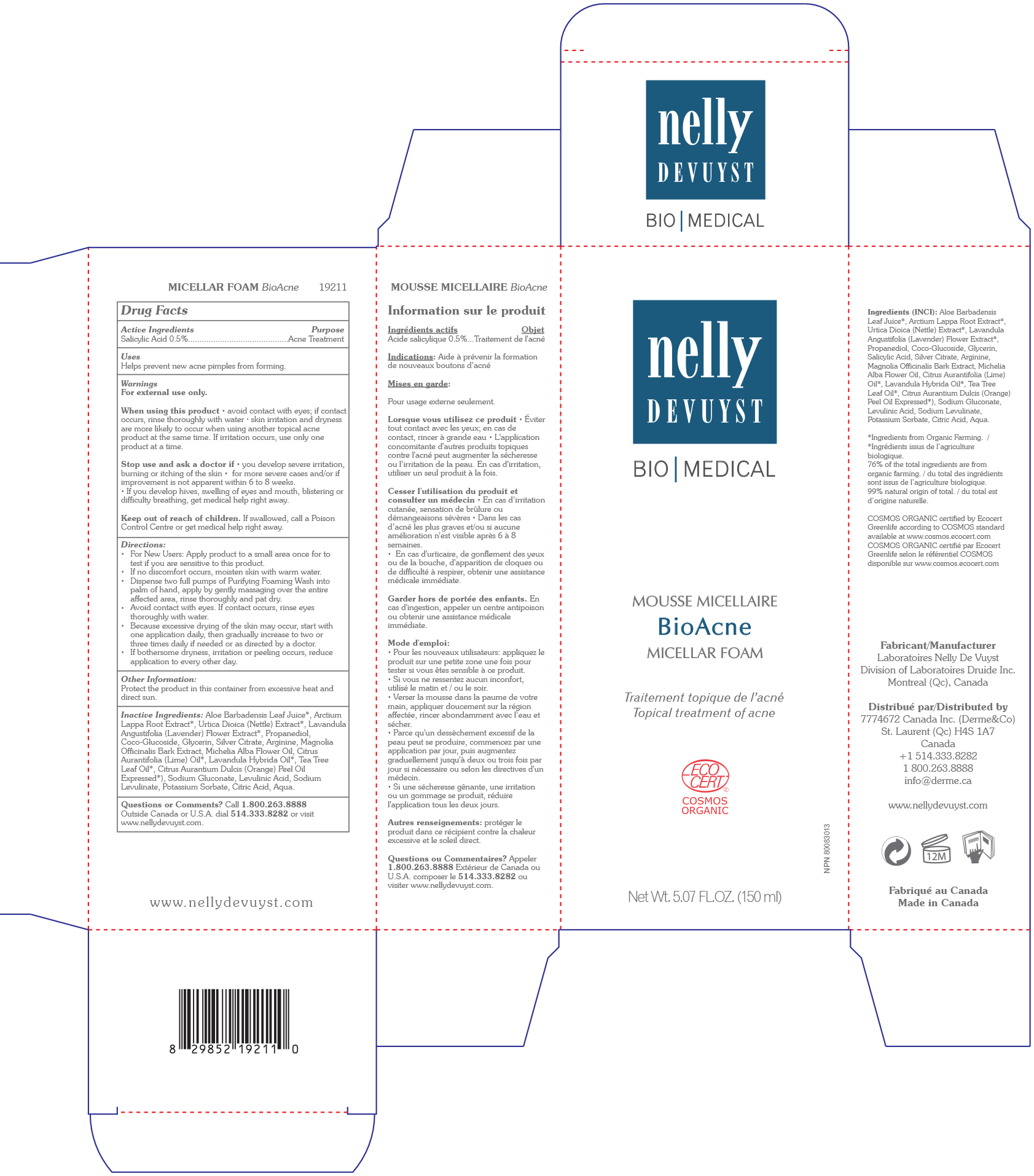 DRUG LABEL: NELLY DEVUYST MICELLAR FOAM BIOACNE
NDC: 71447-008 | Form: LIQUID
Manufacturer: LABORATOIRES DRUIDE INC
Category: otc | Type: HUMAN OTC DRUG LABEL
Date: 20210101

ACTIVE INGREDIENTS: SALICYLIC ACID 0.5 g/100 mL
INACTIVE INGREDIENTS: LIME OIL; TEA TREE OIL; SODIUM GLUCONATE; LEVULINIC ACID; SODIUM LEVULINATE; POTASSIUM SORBATE; CITRIC ACID MONOHYDRATE; URTICA DIOICA LEAF; LAVANDULA ANGUSTIFOLIA FLOWER; WATER; ALOE VERA LEAF; ARCTIUM LAPPA ROOT OIL; COCO GLUCOSIDE; GLYCERIN; SILVER CITRATE; ARGININE; MAGNOLIA OFFICINALIS BARK; PROPANEDIOL; MICHELIA ALBA LEAF OIL; LAVANDIN OIL; CITRUS AURANTIUM FRUIT OIL

NELLY DEVUYST MICELLAR FOAM BIOACNE 150mL

Active Ingredients

Salicylic acid 0.5%

Purpose

Acne Treatment

Uses

Helps prevent new acne pimples from forming.

Warnings

For external use only.

When using this product

▪ avoid contact with eyes. If contact occurs, rinse thoroughly with water ▪ Skin irritation and dryness are more likely to occur when using another topical acne product at the same time. If irritation occurs, use only one product at a time.

and ask a doctor if

▪ you develop severe irritation, burning or itching of the skin ▪ for more severe cases and or if improvement is not apparent within 6 to 8 weeks ▪ If you develop hives, swelling of eyes and mouth, blistering or difficulty breathing, get medical help right away.

Keep out of reach of children.

If swallowed, get medical help or contact a Poison Control Center right away.

Directions

▪ For new users: apply product to a small area once to test if you are sensitive to this product.

▪ If no discomfort occurs, moisten skin with warm water.

▪ Dispense two full pumps of product into palm of hand, apply by gently massaging over the entire affected area, rinse thoroughly and pat dry.

▪ Avoid contact with eyes. If contact occurs, rinse eyes with water.

▪ Because excessive drying of the skin may occur, start with one application daily, then gradually increase to two or three times daily if needed or as directed by a doctor.

▪ If bothersome dryness, irritation or peeling occurs, reduce application to every other day.

Other information

Protect the product in this container from excessive heat and direct sun.

Inactive Ingredients

Aloe Barbadensis Leaf Juice*, Arctium Lappa Root Extract*, Urtica Dioica (Nettle) Extract*, Lavandula Angustifolia (Lavender) Flower Extract*, Propanediol, Coco-Glucoside, Glycerin, Silver Citrate, Arginine, Magnolia Officinalis Bark Extract, Michelia Alba Flower Oil, Citrus Aurantifolia (Lime) Oil*, Lavandula Hybrida Oil*, Tea Tree Leaf Oil*, Citrus Aurantium Dulcis (Orange) Peel Oil Expressed*, Sodium Gluconate, Levulinic Acid, Sodium Levulinate, Potassium Sorbate, Citric Acid, Aqua.

Certified organic*

Questions or Comments?

Call +1 800-263-8888

Outside Canada or United States, dial +1 514-333-8282, or visit www.nellydevuyst.com

Distributed By

7774672 Canada Inc (Derme & Co)

4980 Chemin Bois Franc

St. Laurent, QC H4S 1A7

Canada

+1 514-333-8282, +1 800-263-8888

www.nellydevuyst.com

Made in Canada